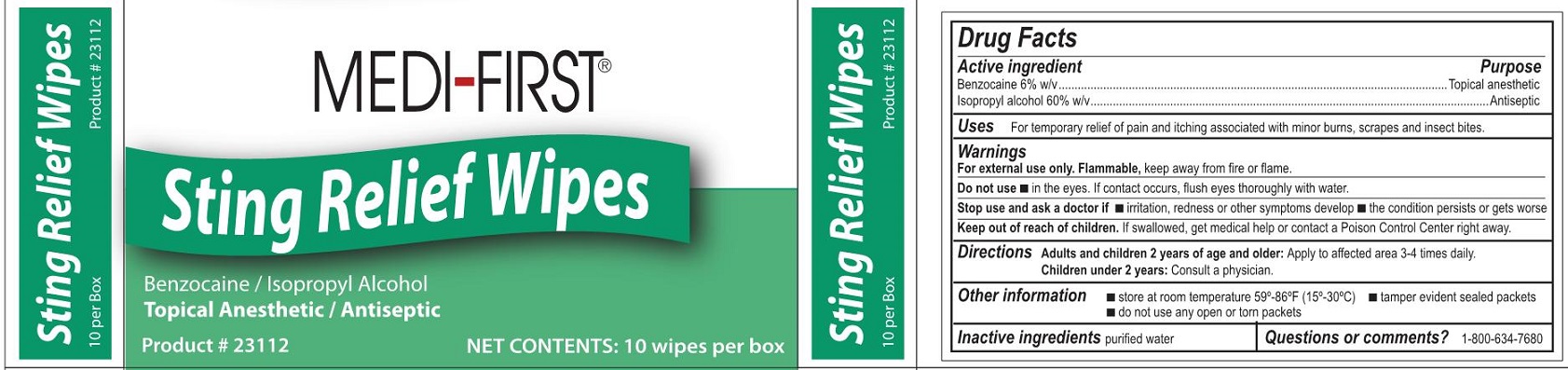 DRUG LABEL: Medi-First Sting Relief
NDC: 47682-234 | Form: SWAB
Manufacturer: Unifirst First Aid Corporation
Category: otc | Type: HUMAN OTC DRUG LABEL
Date: 20250908

ACTIVE INGREDIENTS: BENZOCAINE 60 mg/1 mL; ISOPROPYL ALCOHOL 0.6 mL/1 mL
INACTIVE INGREDIENTS: WATER

Medi-First Sting Relief Wipes

Active ingredient

Benzocaine 6% w/v

Isopropyl alcohol 60% w/v

Purpose

Topical anesthetic

Antiseptic

Uses

For temporary relief of pain and itching associated with minor burns, scrapes and insect bites.

Warnings

For external use only.

Flammable, keep away from fire or flame.

Do not use

- in the eyes. If contact occurs, rinse thoroughly with water.

Stop use and ask a doctor if

- irritation, redness or other symptoms develop
- the condition persists or gets worse

Keep out of reach of children.

If swallowed, get medical help or contact a Poison Control Center right away.

Directions

Adults and children 2 years of age and older: Apply to affected area 3-4 times daily.

Children under 2 years: CXonsult physician.

Other information

- store at room temperature 59º-86ºF (15º-30ºC)
- tamper evident sealed packets
- do not use any opened or torn packets

Inactive ingredients

purified water

Questions or comments?

1-800-634-7680

Medi-First Sting Relief Wipes Label

Medi-First®

Sting Relief Wipes

Benzocaine/ Isopropyl Acohol

Topical Anesthetic/ Antiseptic

Product # 23112

NET CONTENTS: 10 wipes per box